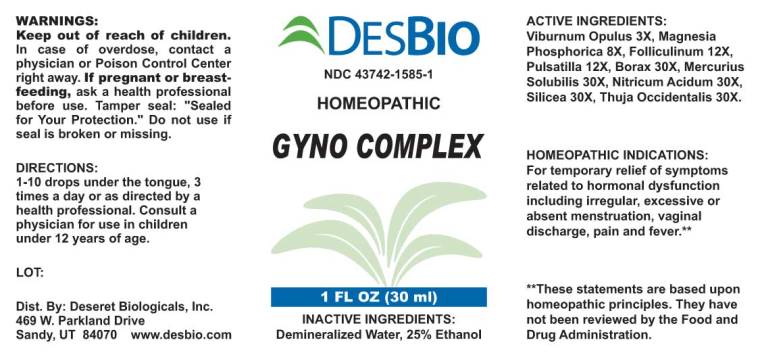 DRUG LABEL: Gyno Complex
NDC: 43742-1585 | Form: LIQUID
Manufacturer: Deseret Biologicals, Inc
Category: homeopathic | Type: HUMAN OTC DRUG LABEL
Date: 20230112

ACTIVE INGREDIENTS: VIBURNUM OPULUS BARK 3 [hp_X]/1 mL; MAGNESIUM PHOSPHATE, DIBASIC TRIHYDRATE 8 [hp_X]/1 mL; ESTRONE 12 [hp_X]/1 mL; ANEMONE PRATENSIS 12 [hp_X]/1 mL; SODIUM BORATE 30 [hp_X]/1 mL; MERCURIUS SOLUBILIS 30 [hp_X]/1 mL; NITRIC ACID 30 [hp_X]/1 mL; SILICON DIOXIDE 30 [hp_X]/1 mL; THUJA OCCIDENTALIS LEAF 30 [hp_X]/1 mL
INACTIVE INGREDIENTS: WATER; ALCOHOL

Drug Facts:

ACTIVE INGREDIENTS:

Viburnum Opulus 3X, Magnesia Phosphorica 8X, Folliculinum 12X, Pulsatilla (Pratensis) 12X, Borax 30X, Mercurius Solubilis 30X, Nitricum Acidum 30X, Silicea 30X, Thuja Occidentalis 30X.

HOMEOPATHIC INDICATIONS:

For temporary relief of symptoms related to hormonal dysfunction including irregular, excessive or absent menstruation, vaginal discharge, pain and fever.**

**These statements are based upon traditional homeopathic principles. They have not been reviewed by the Food and Drug Administration.

WARNINGS:

Keep out of reach of children. In case of overdose, contact physician or Poison Control Center right away.

If pregnant or breast-feeding, ask a health professional before use.

Tamper seal: "Sealed for Your Protection."

Do not use if seal is broken or missing.

Keep out of reach of children. In case of overdose, contact physician or Poison Control Center right away.

DIRECTIONS:

1-10 drops under the tongue, 3 times a day or as directed by a health professional. Consult a physician for use in children under 12 years of age.

HOMEOPATHIC INDICATIONS:

For temporary relief of symptoms related to hormonal dysfunction including irregular, excessive or absent menstruation, vaginal discharge, pain and fever.**

**These statements are based upon traditional homeopathic principles. They have not been reviewed by the Food and Drug Administration.

INACTIVE INGREDIENTS:

Demineralized Water, 25% Ethanol

QUESTIONS:

Dist. By: Deseret Biologicals, Inc.

469 W. Parkland Drive

Sandy, UT 84070

www.desbio.com

PACKAGE LABEL DISPLAY:

DESBIO

NDC 43742-1585-1

HOMEOPATHIC

GYNO COMPLEX

1 FL OZ (30 mL)